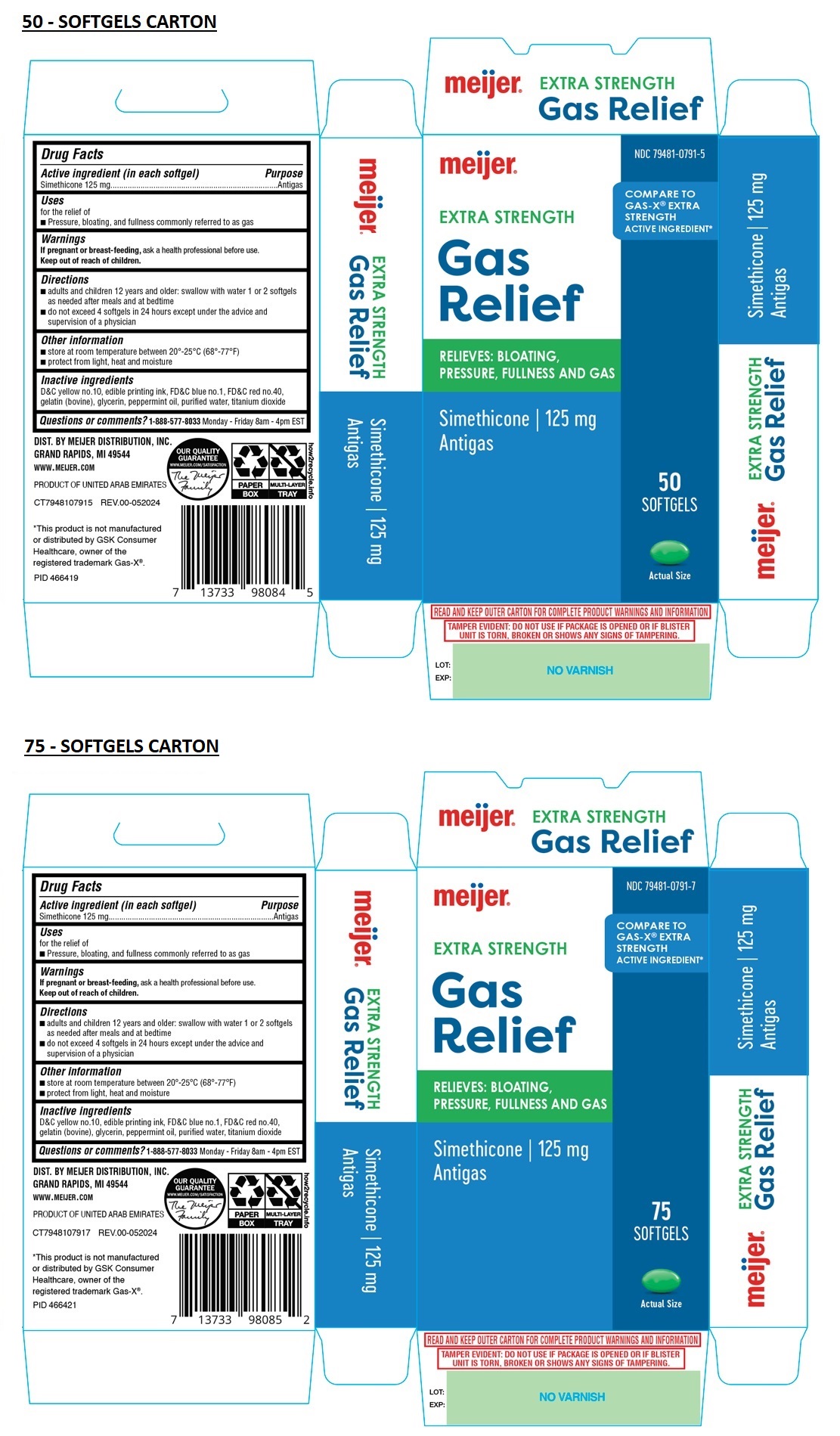 DRUG LABEL: meijer EXTRA STRENGTH Gas Relief SOFTGEL
NDC: 79481-0791 | Form: CAPSULE, LIQUID FILLED
Manufacturer: Meijer, Inc.
Category: otc | Type: HUMAN OTC DRUG LABEL
Date: 20240912

ACTIVE INGREDIENTS: DIMETHICONE, UNSPECIFIED 125 mg/1 1
INACTIVE INGREDIENTS: D&C YELLOW NO. 10; FD&C BLUE NO. 1; FD&C RED NO. 40; GELATIN TYPE B BOVINE (230 BLOOM); GLYCERIN; PEPPERMINT OIL; WATER; TITANIUM DIOXIDE

meijer EXTRA STRENGTH Gas Relief SOFTGEL

Active ingredient (in each softgel)

Simethicone 125 mg

Purpose

Antigas

Uses

for the relief of
• Pressure, bloating, and fullness commonly referred to as gas

Warnings

If pregnant or breast-feeding, ask a health professional before use.

Keep out of reach of children.

Directions

• adults and children 12 years and older: swallow with water 1 or 2 softgels as needed after meals and at bedtime
• do not exceed 4 softgels in 24 hours except under the advice and supervision of a physician

Other information

• store at room temperature between 20°-25°C (68°-77°F)
• protect from light, heat and moisture

Inactive ingredients

D&C yellow no.10, edible printing ink, FD&C blue no.1, FD&C red no. 40, gelatin (bovine), glycerin, peppermint oil, purified water, titanium dioxide

Questions or comments?

1-888-577-8033 Monday - Friday 8am - 4pm EST

COMPARE TO GAS-X® EXTRA STRENGTH ACTIVE INGREDIENT*

RELIEVES: BLOATING,
PRESSURE, FULLNESS AND GAS

DIST. BY MEIJER DISTRIBUTION, INC.
GRAND RAPIDS, MI 49544

WWW.MEIJER.COM

PRODUCT OF UNITED ARAB EMIRATES

*This product is not manufactured or distributed by GSK Consumer Healthcare, owner of the registered trademark Gas-X®.

READ AND KEEP OUTER CARTON FOR COMPLETE PRODUCT WARNINGS AND INFORMATION

TAMPER EVIDENT: DO NOT USE IF PACKAGE IS OPENED OR IF BLISTER UNIT IS TORN, BROKEN OR SHOWS ANY SIGNS OF TAMPERING.